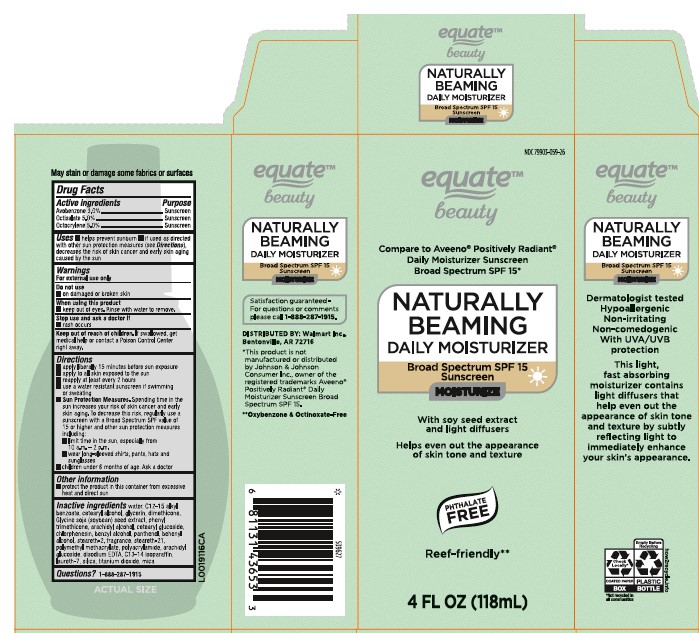 DRUG LABEL: SPF Moisturizer
NDC: 79903-059 | Form: LOTION
Manufacturer: Walmart Inc.
Category: otc | Type: HUMAN OTC DRUG LABEL
Date: 20260227

ACTIVE INGREDIENTS: AVOBENZONE 30 mg/1 mL; OCTISALATE 50 mg/1 mL; OCTOCRYLENE 50 mg/1 mL
INACTIVE INGREDIENTS: WATER; ALKYL (C12-15) BENZOATE; CETOSTEARYL ALCOHOL; GLYCERIN; DIMETHICONE; SOYBEAN; PHENYL TRIMETHICONE; ARACHIDYL ALCOHOL; CETEARYL GLUCOSIDE; CHLORPHENESIN; BENZYL ALCOHOL; PANTHENOL; DOCOSANOL; STEARETH-2; STEARETH-21; POLY(METHYL METHACRYLATE; 450000 MW); POLYACRYLAMIDE (CROSSLINKED; 2 MOLE PERCENT BISACRYLAMIDE); ARACHIDYL GLUCOSIDE; EDETATE DISODIUM ANHYDROUS; C13-14 ISOPARAFFIN; LAURETH-7; SILICON DIOXIDE; TITANIUM DIOXIDE; MICA

Equate 159.000/159AA-AB
Absolutely Beaming Daily Moisturizer

disclaimer

May stain or damage some fabrics or surfaces.

Active ingredients

Avobenzone 3.0%

Octisalate 5.0%

Octocrylene 5.0%

Purpose

Sunscreen

Uses

- helps prevent sunburn
- if used as directed with other sun protection measures (see Directions), decreases the risk of skin cancer and early skin aging caused by the sun

Warnings

For external use only

Do not use

- on damaged or broken skin

When using this product

- keep out of the eyes. Rinse with water to remove.

Stop use and ask a doctor if

- rash occurs

Keep out of reach of children

If swallowed, get medical help or contact a Poison Control Center right away.

Directions

■ apply liberally 15 minutes before sun exposure
■ apply to all skin exposed to the sun
■ reapply at least every 2 hours
■ use a water resistant sunscreen if swimming or sweating
■ Sun Protection Measures.Spending time in the sun increases your risk of skin cancer and early skin aging. To decrease this risk, regularly use a sunscreen with a Broad Spectrum SPF value of 15 or higher and other sun protection measures including:
■ limit time in the sun, especially from 10 a.m.–2 p.m.
■ wear long-sleeved shirts, pants, hats and sunglasses
■ children under 6 months of age: Ask a doctor

Other information

- protect the product in this container from excessive heat and direct sun

inactive ingredients

water, C12-15 alkyl benzoate, cetearyl alcohol, glycerin, dimethicone, Glycine soja (soybean) seed extract, phenyl trimethicone, arachidyl alcohol, cetearyl glucoside, chlorphenesin, benzyl alcohol, panthenol, behenyl alcohol, steareth-2, fragrance, steareth-21, polymethyl methacrylate, polyacrylamide, arachidyl glucoside, disodium EDTA, C13-14 isoparaffin, laureth-7, silica, titanium dioxide, mica

Questions?

1-888-287-1915

Adverse Reactions

Satisfaction guaranteed - For questions or comments please call 1-888-287-1915

DISTRIBUTED BY: Walmart Inc., Bentonville, AR 72716

*This product is not manufactured or distributed by Johnson & Johnson Consumer Inc., owner of the registered trademarks Aveeno®Positively RadiantDaily Moisturizer Sunscreen Broad Spectrum SPF 15.

** Oxybenzone & Octinoxate- Free

Side Panel

equate

beauty

NATURALLY BEAMING

DAILY MOISTURIZER

Broad Spectrum SPF 15 Sunscreen

MOISTURIZE

Dermatologist tested

Hypoallergenic

Non-irritating

Non-comedogenic

With UVA/UVB protection

This light, fast absorbing moisturizer contains light diffusers that help even out the appearance of skin tone and texture by subtly reflecting light to immediately enhance yor skin's appearance.

Check Locally*

COATED PAPER BOX

*Not recycled in all communities

Empty Before Recycling

PLASTIC BOTTLE

how2recycle.org

Principal display panel

NDC 79903-059-26

equate™

beauty

Compare to Aveeno®Positively Radiant®Daily Moisturizer Sunscreen Broad Spectrum SPF 15*

NATURALLY BEAMING

DAILY MOISTURIZER

Broad Spectrum SPF 15

Sunscreen

MOISTURIZE

With soy seed extract and light diffusers

Helps even out the appearance of skin tone and texture

PHTHALATE FREE

Reef-friendly**

4 FL OZ (118 mL)